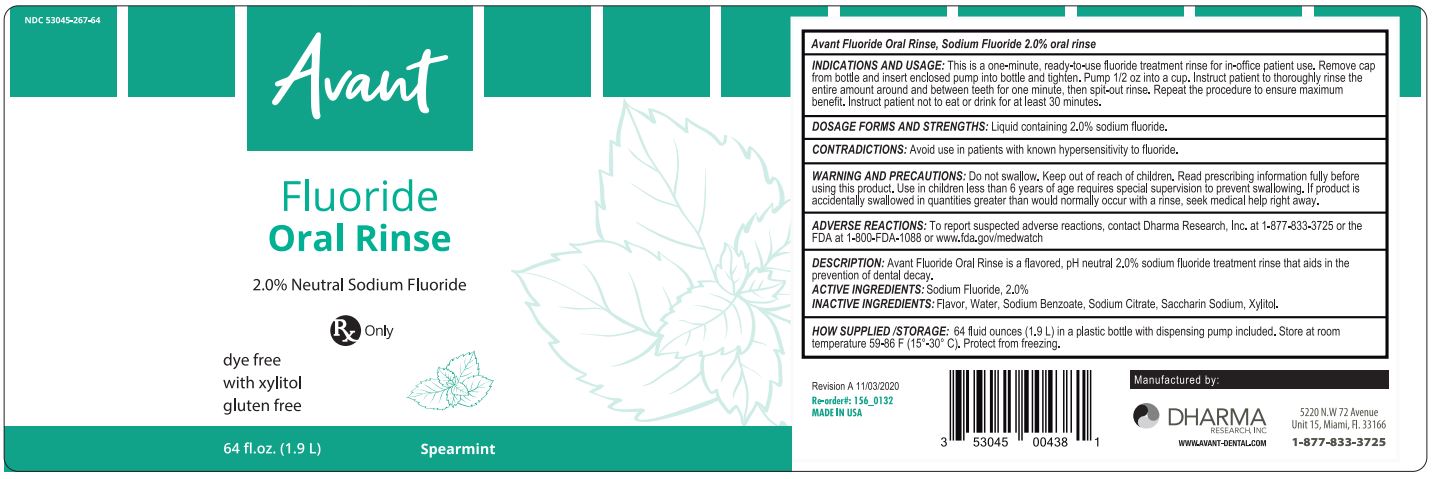 DRUG LABEL: Avant
NDC: 53045-267 | Form: LIQUID
Manufacturer: Dharma Research, Inc.
Category: prescription | Type: HUMAN PRESCRIPTION DRUG LABEL
Date: 20210125

ACTIVE INGREDIENTS: SODIUM FLUORIDE 2 g/1 L
INACTIVE INGREDIENTS: WATER; SODIUM BENZOATE; SACCHARIN SODIUM; XYLITOL

INDICATIONS AND USAGE

This is a one-minute, ready-to-use fluoride treatment rinse for in-office patient use. Remove cap from bottle and insert enclosed pump into bottle and tighten. Pump ½ oz into a cup. Instruct patient to thoroughly rinse the entire amount around and between teeth for one minute, then spit-out rinse. Repeat the procedure to ensure maximum benefit. Instruct patient not to eat or drink for at least 30 minutes.

DOSAGE FORM AND STRENGTH

Liquid containing 2% sodium fluoride

CONTRAINDICATIONS

Avoid use in patients with known hypersensitivity to fluoride

WARNINGS AND PRECAUTIONS

Do not swallow. Keep out of reach of children. Read prescribing information fully before using this product. Use in children less than 6 years of age requires special supervision to prevent swallowing. If product is accidentally swallowed in quantities greater than would normally occur with a rinse, seek medical help right away.

ADVERSE REACTIONS

To report suspected adverse reactions, contact Dharma Research, Inc. at 1-877-833-3725 or the FDA at 1-800-FDA-1088 or www.fda.gov/medwatch

DESCRIPTION

Avant Fluoride Oral Rinse is a flavored, pH neutral 2.0% sodium fluoride treatment rinse that aids in the prevention of dental decay.

ACTIVE INGREDIENT: Sodium Fluoride, 2.0%

INACTIVE INGREDIENTS: Flavor, Water, Sodium Benzoate, Sodium Citrate, Saccharin Sodium, Xylitol

HOW SUPPLIED/STORAGE

64 fluid ounces (1.9 L) in a plastic bottle with dispensing pump included. Store at room temperature 59-86°F (15-30°C). Protect from freezing.

Avant Sodium Fluoride Oral Rinse

2.0% Neutral Sodium Fluoride

Rx Only

Dye Free

With Xylitol

Gluten Free

64 fl. oz. (1.9 L)

Spearmint

Manufactured by:

Dharma Research, Inc., 5220 NW 72nd Avenue, Unit 15, Miami, FL, 33166

1-877-833-3725

www.avant-dental.com

Label Revision A, 11/03/2020